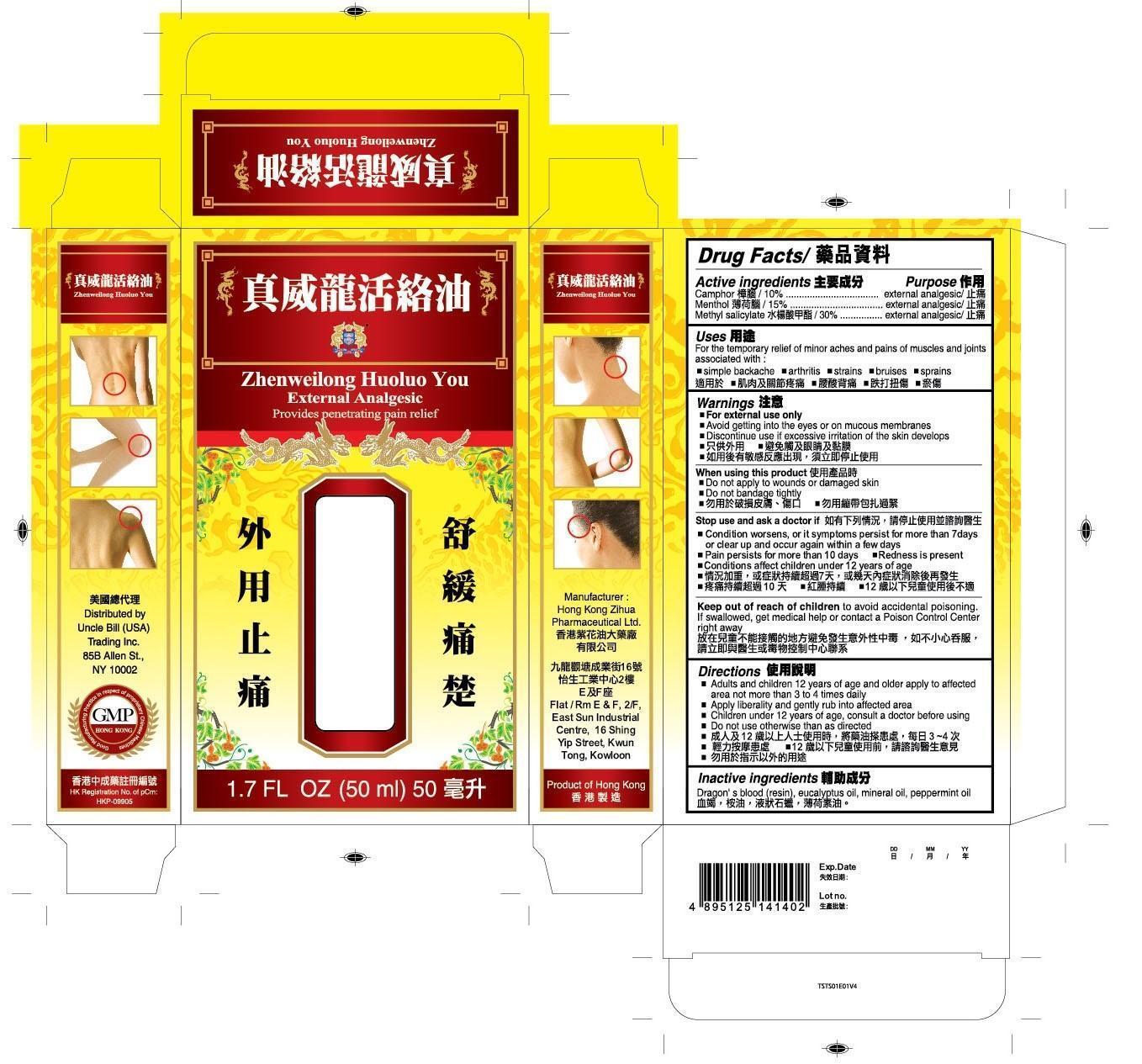 DRUG LABEL: Zhenweilong Huoluo You
NDC: 49980-001 | Form: OIL
Manufacturer: Hong Kong Zihua Pharmaceutical Ltd.
Category: otc | Type: HUMAN OTC DRUG LABEL
Date: 20141023

ACTIVE INGREDIENTS: CAMPHOR (NATURAL) 10 g/100 mL; MENTHOL 15 g/100 mL; METHYL SALICYLATE 30 g/100 mL
INACTIVE INGREDIENTS: DRAGON'S BLOOD; EUCALYPTUS OIL; MINERAL OIL; PEPPERMINT OIL

Drug Facts

Active Ingredients

Camphor 10%

Menthol 15%

Methyl Salicylate 30%

Purpose

external analgesic

external analgesic

external analgesic

Uses

For the temporary relief of minor aches and pains of muscles and joints associated with:

■ simple backache ■ arthritis ■ strains ■ bruises ■ sprains

Warnings

■ For external use only

■ Avoid getting into the eyes or on mucous membranes

■ Discontinue use if excessive irritation of the skin develops

When using this product

■ Do not apply to wound or damaged skin.

■ Do not bandage tightly

Stop use and ask a doctor if

■ Condition worsens, or if symptoms persist for more than 7 days or clear up and occur again within a few days

■ Pain persists for more than 10 days conditions ■ Redness is present ■ Conditions affect children under 12 years of age

Keep out of reach of children

to avoid accidental poisoning. If swallowed, get medical help or contact a poison control center right away.

Directions

■ Adults and children 12 years of age and older apply to affected area not more than 3 to 4 time daily.

■ Children under 12 years of age, consult a doctor before using

■ Do not use otherwise than as directed

Inactive ingredients

Dragon's blood (resin), eucalyptus oil, mineral oil, peppermint oil